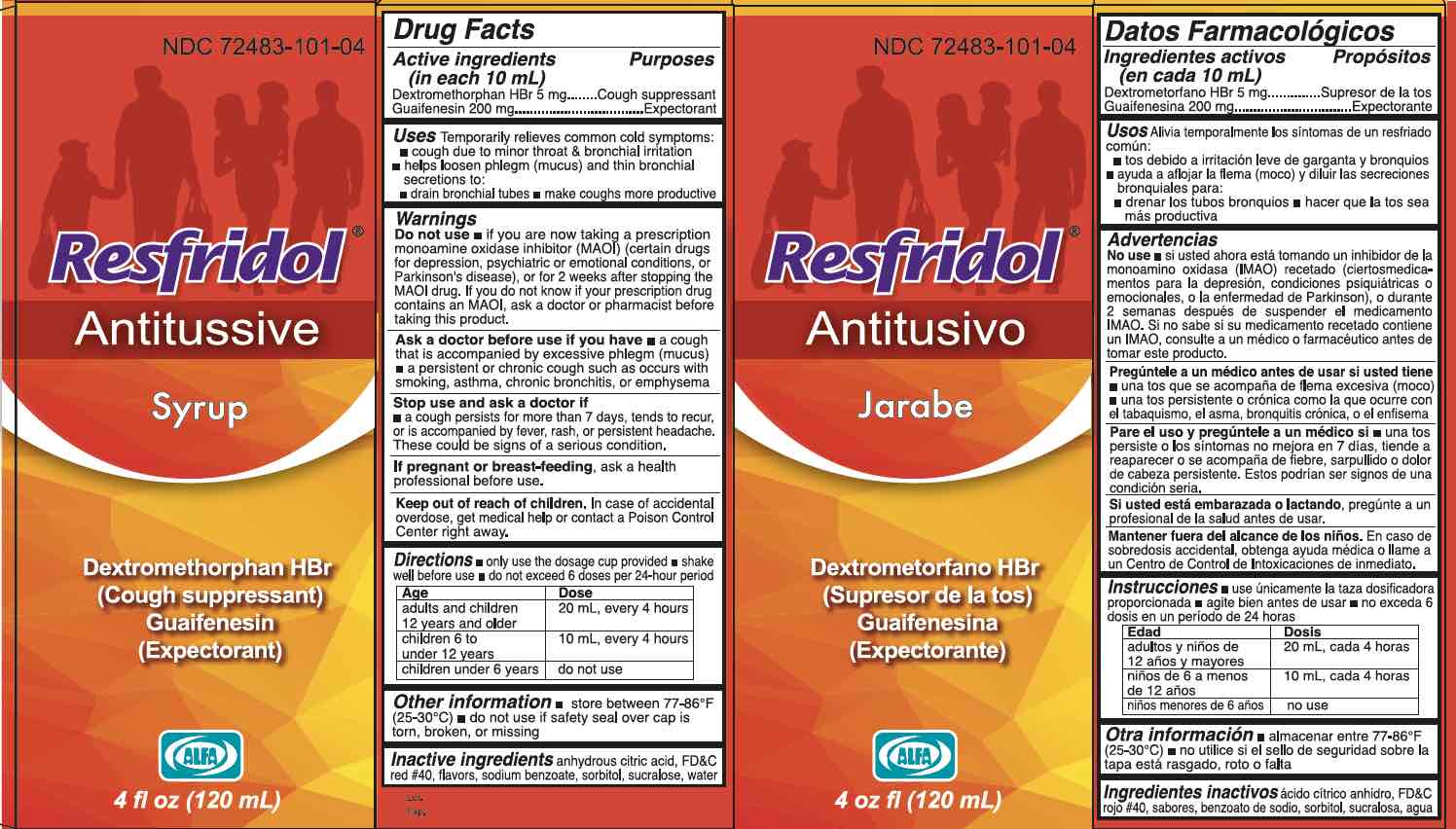 DRUG LABEL: Resfridol
NDC: 72483-101 | Form: SYRUP
Manufacturer: Laboratorios Alfa
Category: otc | Type: HUMAN OTC DRUG LABEL
Date: 20251229

ACTIVE INGREDIENTS: DEXTROMETHORPHAN HYDROBROMIDE 5 mg/10 mL; GUAIFENESIN 200 mg/10 mL
INACTIVE INGREDIENTS: SUCRALOSE; WATER; SORBITOL; ANHYDROUS CITRIC ACID; FD&C RED NO. 40; SODIUM BENZOATE

Resfridol Antitussive (NEW)

Active ingredients and Purposes

PURPOSE

Active ingredients (in each 10 mL) | Purposes
Dextromethorphan HBr 5 mg ............................................................................ | Cough suppressant
Guaifenesin 200 mg........................................................................................... | Expectorant

Uses

Temporarily relieves common cold symptoms:

- cough due to minor throat & bronchial irritation
- helps loosen phlegm (mucus) and thin bronchial secretions to:
- drain bronchial tubes
- make coughs more productive

Warnings

Do not use

- if you are now taking a prescription monoamine oxidase inhibitor (MAOI) (certain drugs for depression, psychiatric or emotional conditions, or Parkinson's disease), or for 2 weeks after stopping the MAOI drug. If you do not know if your prescription drug contains an MAOI, ask a doctor or pharmacist before taking this product.

Stop use and ask a doctor if

■ a cough persists for more than 7 days, tends to recur, or is accompanied by fever, rash, or persistent headache. These could be signs of a serious condition.

Ask a doctor before use if you have

■a cough that is accompanied by excessive phlegm (mucus)

■ a persistent or chronic cough such as occurs with smoking, asthma, chronic bronchitis, or emphysema

If pregnant or breast-feeding,

ask a health professional before use.

Keep out of reach of children.

In case of accidental overdose, get medical help or contact a Poison Control Center right away.

Directions

■ only use the dosage cup provided

■ shake well before use

■ do not exceed 6 doses per 24-hour period

Age | Dose
adults and children 12 years and older | 20 mL, every 4 hours
children 6 to under 12 years | 10 mL, every 4 hours
children under 6 years | do not use

Other information

■ store between 68-77°F (20-25°C)

■ do not use if safety seal over cap is torn, broken, or missing

Inactive ingredients

anhydrous citric acid, FD&C red #40, flavors, sodium benzoate, sorbitol, sucralose, water

Questions?

+1-809-544-0222

(M-F) 9 AM - 5 PM EST or www.laboratoriosalfa.com